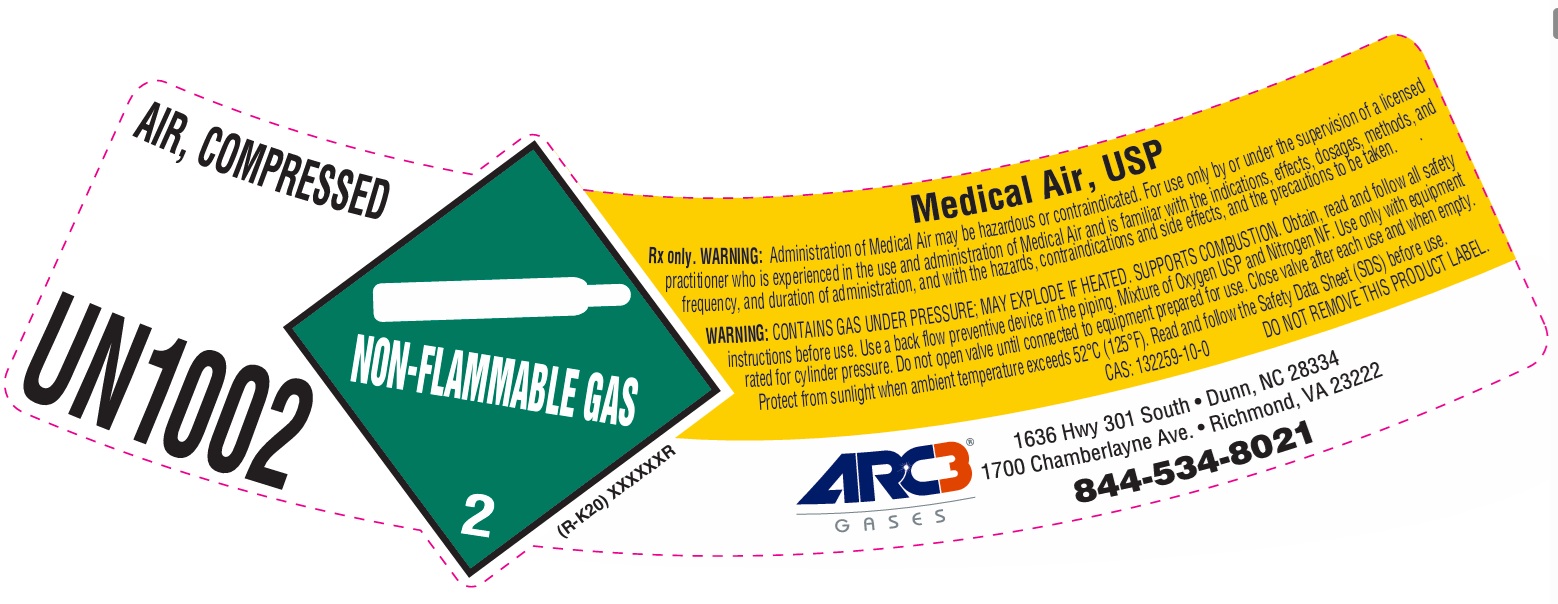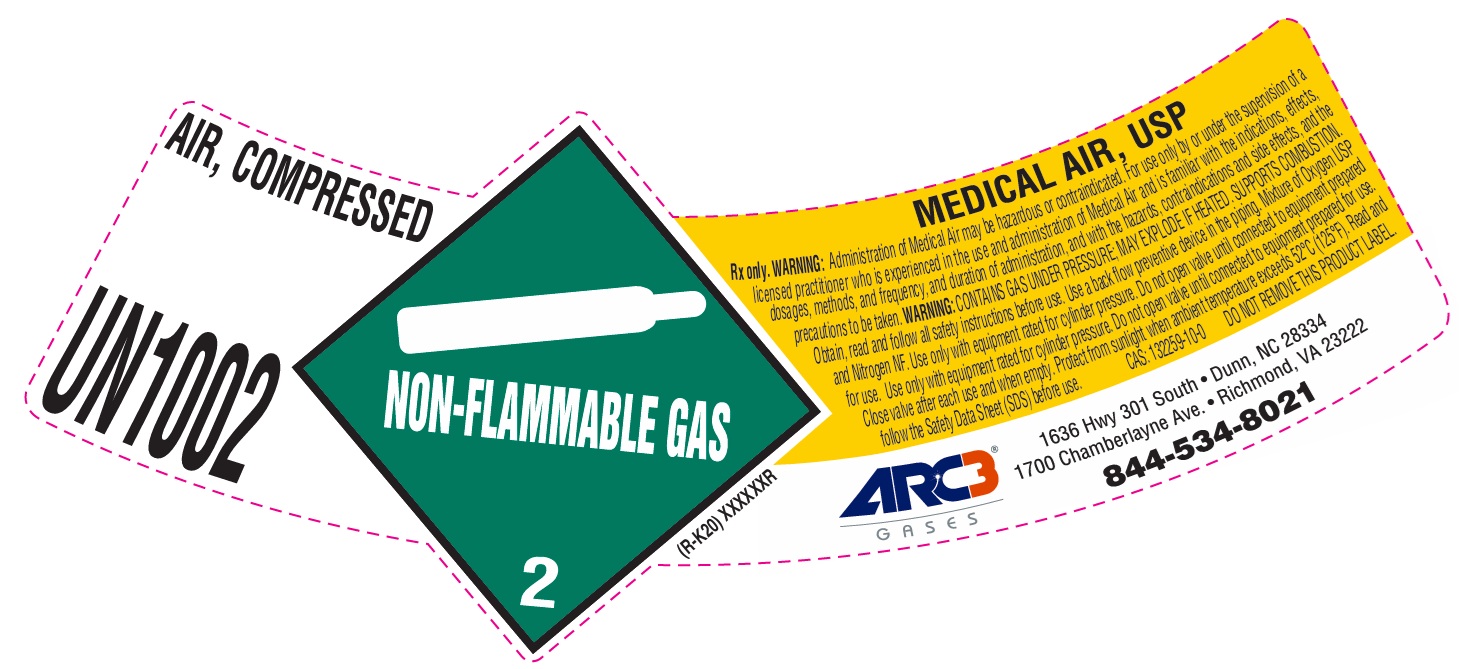 DRUG LABEL: Air
NDC: 49575-004 | Form: GAS
Manufacturer: Machine & Welding Supply Company dba Arc3 Gases South
Category: prescription | Type: HUMAN PRESCRIPTION DRUG LABEL
Date: 20251202

ACTIVE INGREDIENTS: AIR 1000 mL/1 L

Medical Air Label

PACKAGE LABEL

AIR, COMPRESSED

UN1002

Medical Air, USP

Rx only. WARNING: Administration of Medical Air may be hazardous or contraindicated. For use only by or under the supervision of a licensed practitioner who is experienced in the use and administration of Medical Air and is familiar with the indications, effects, dosages, methods, and frequency, and duration of administration, and with the hazards, contraindications and side effects, and the precautions to be taken.

WARNING: CONTAINS GAS UNDER PRESSURE; MAY EXPLODE IF HEATED. SUPPORTS COMBUSTION. Obtain, read and follow all safety instructions before use. Use a back flow preventive device in the piping. Mixture of Oxygen and Nitrogen NF. Use only with equipment rated for cylinder pressure. Do not open valve until connected to equipment prepared for use. Close valve after each use and when empty. Protect from sunlight when ambient temperature exceeds 52 C (125 F). Read and follow the Safety Data Sheet (SDS) before use.

CAS: 132259-10-0 DO NOT REMOVE THIS PRODUCT LABEL.

ARC3 GASES

1636 Hwy 301 South Dunn, NC 28334

1700 Chamberlayne Ave. Richmond, VA 23222

844-534-8021

PACKAGE LABEL

AIR, COMPRESSED

UN1002

MEDICAL AIR, USP

Rx only. WARNING: Administration of Medical Air may be hazardous or contraindicated. For use only by or under the supervision of a licensed practitioner who is experienced in the use and administration of Medical Air and is familiar with the indications, effects, dosages, methods, and frequency, and duration of administration, and with the hazards, contraindications and side effects, and the precautions to be taken. WARNING: CONTAINS GAS UNDER PRESSURE; MAY EXPLODE IF HEATED. SUPPORTS COMBUSTION. Obtain, read and follow all safety instructions before use. Use a back flow preventive device in the piping. Mixture of Oxygen USP and Nitrogen NF. Use only with equipment rated for cylinder pressure. Do not open valve until connected to equipment prepared for use. Use only with equipment rated for cylinder pressure. Do not open valve until connected to equipment prepared for use. Close valve after each use and when empty. Protect from sunlight when ambient temperature exceeds 52 C (125 F). Read and follow the Safety Data Sheet (SDS) before use. CAS: 132259-10-0 DO NOT REMOVE THIS PRODUCT LABEL.

ARC3 GASES

1636 Hwy 301 South Dunn, NC 28334

1700 Chamberlayne Ave. Richmond, VA 23222

844-534-8021